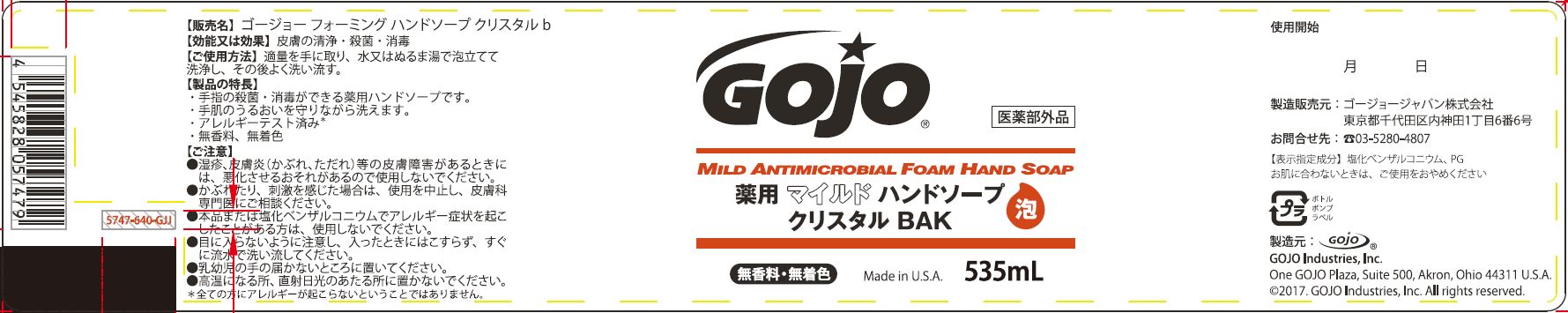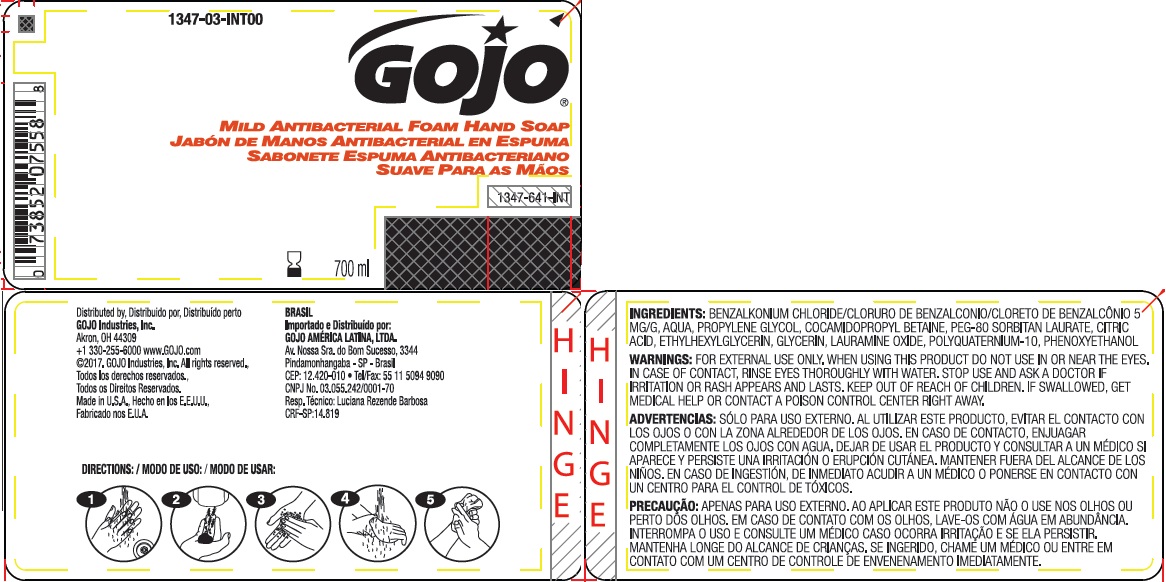 DRUG LABEL: GOJO Mild Antibacterial Foam Hand Sp
NDC: 21749-051 | Form: LIQUID
Manufacturer: GOJO Industries, Inc.
Category: otc | Type: HUMAN OTC DRUG LABEL
Date: 20241231

ACTIVE INGREDIENTS: BENZALKONIUM CHLORIDE 0.005 mg/1 mL
INACTIVE INGREDIENTS: WATER; PROPYLENE GLYCOL; COCAMIDOPROPYL BETAINE; PEG-80 SORBITAN LAURATE; CITRIC ACID MONOHYDRATE; ETHYLHEXYLGLYCERIN; GLYCERIN; LAURAMINE OXIDE; POLYQUATERNIUM-10 (10000 MPA.S AT 2%); PHENOXYETHANOL

GOJO Mild Antibacterial Foam Hand Soap